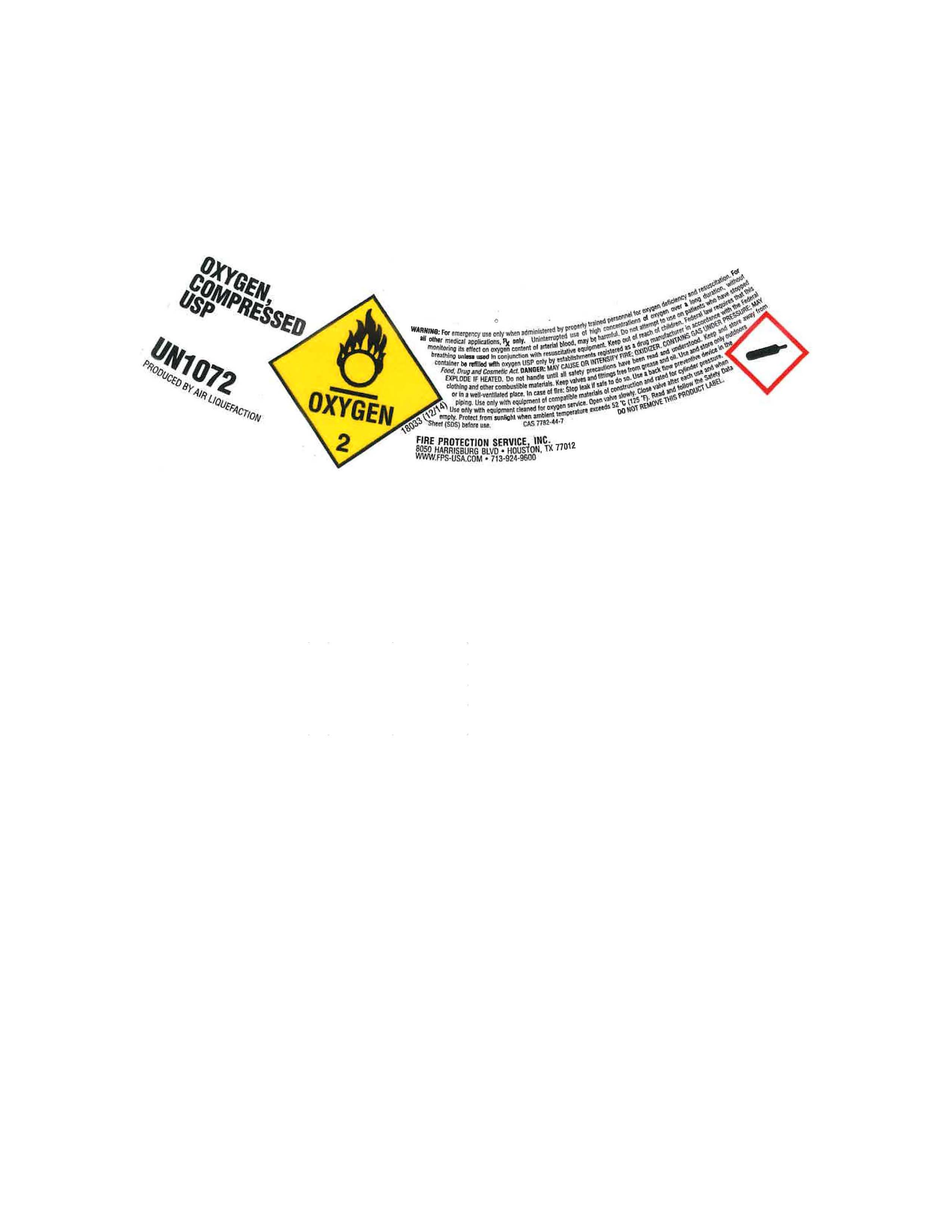 DRUG LABEL: Oxygen
NDC: 67515-001 | Form: GAS
Manufacturer: Fire Protection Service, Inc.
Category: prescription | Type: HUMAN PRESCRIPTION DRUG LABEL
Date: 20260113

ACTIVE INGREDIENTS: OXYGEN 990 mL/1 L

Medical Oxygen

OXYGEN, COMPRESSED USP

UN1072

PRODUCED BY AIR LIQUIEFACTION

Medical Oxygen

Compressed Oxygen

Warning

For emergency use only when administered by properly trained personnel for oxygen deficiency and resuscitation. For all other medical applications, Rx ONLY. Uninterrupted use of high concentrations of oxygen over a long duration, without monitoring its effect on oxygen content of arterial blood, may be harmful. Do not attempt to use on patients who have stopped breathing unless used in conjuction with resuscitative equipment. Keep out of reach of children. Federal law requires that this container be refilled with oxygen USP only by establishments registered as a drug manufacturer in accordance with the Federal Food, Drug and cosmetic Act. DANGER: MAY CAUSE OR INTENSIFY FIRE; OXIDIZER CONTAINS GAS UNDER PRESSURE; MAY EXPLODE IF HEATED. Do not handle until all safety precaustions have been read and understood. Keep and store away from clothing and other combustible materials. Keep valves and fittings free from grease and oil. Use and store only outdoors or in a well-ventilated place. In case of fire, stop leak if safe to do so. UUse a back flow preventive device in the piping. Use only with equipment of combustible materials of construction and rated for cylinder pressure. Use only with equipment cleaned for Oxygen service and rated for cylinder pressure. Open valve slowly. Close valve after each use and when empty. Protect from sunlight when ambient temperature exceeds 52 C (125F). Read and follow the Safety Data Sheet (SDS) before use. CAS 7782-44-7 DO NOT REMOVE THIS PRODUCT LABEL.

Fire Protection Service, Inc. 8050 Harrisburg Blvd. Houston TX 77012 WWW.FPS-USA.COM 713-924-9600